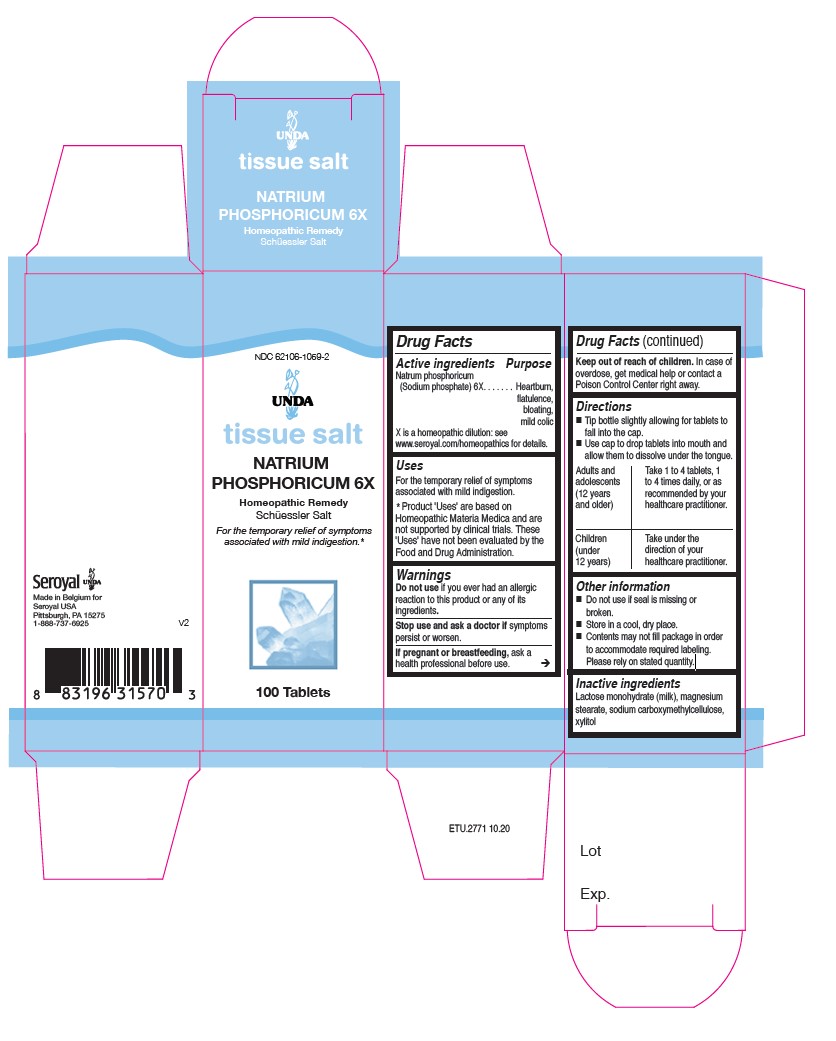 DRUG LABEL: NATRIUM PHOSPHORICUM 6X
NDC: 62106-1059 | Form: TABLET
Manufacturer: Seroyal USA
Category: homeopathic | Type: HUMAN OTC DRUG LABEL
Date: 20210714

ACTIVE INGREDIENTS: SODIUM PHOSPHATE 6 [hp_X]/1 1
INACTIVE INGREDIENTS: LACTOSE MONOHYDRATE; XYLITOL; CROSCARMELLOSE SODIUM; MAGNESIUM STEARATE

NATRIUM PHOSPHORICUM 6X

Active ingredients

Natrum Phosphoricum (Sodium Phosphate) 6X

Uses
For the temporary relief of symptoms associated with mild indigestion.

Warnings
Do not use if you ever had an allergic
reaction to this product or any of its
ingredients.
Stop use and ask a doctor if symptoms
persist or worsen.
If pregnant or breastfeeding, ask a
health professional before use.

Keep out of reach of children. In case of
overdose, get medical help or contact a
Poison Control Center right away

PREGNANCY OR BREAST FEEDING

If you are pregnant or breastfeeding, ask a healthcare practitioner before use.

Keep out of reach of children.

OVERDOSAGE

In case of overdose, get medical help or contact a Poison Control Center right away.

Stop use and ask a doctor if symptoms persist or worsen.

Inactive ingredients
Lactose monohydrate (milk), magnesium
stearate, sodium carboxymethylcellulose,
xylitol

Directions
Tip bottle slightly allowing for tablets to fall into the cap.
Use cap to drop tablets into mouth and allow them to dissolve under the tongue.

Adults and adolescents (12 years and older)

Take 1 to 4 tablets, one to four times daily, or as recommended by your healthcare practitioner.

Children (under 12 years)

Take under the direction of your healthcare practitioner.

Uses
For the temporary relief of symptoms
associated with mild indigestion.

Directions
Tip bottle slightly allowing for tablets to fall into the cap.
Use cap to drop tablets into mouth and allow them to dissolve under the tongue.

Adults and adolescents (12 years and older)

Take 1 to 4 tablets, one to four times daily, or as recommended by your healthcare practitioner.

Children (under 12 years)

Take under the direction of your healthcare practitioner.

Do not use if seal is missing or
broken.
Store in a cool, dry place.
Contents may not fill package in order
to accommodate required labeling.
Please rely on stated quantity.

PACKAGE LABEL

NDC 62106-1059-2

UNDA
tissue salt
NATRIUM PHOSPHORICUM 6X
Homeopathic Remedy
Schuessler salt

For the temporary relief of symptoms associated with mild indigestion

100 Tablets